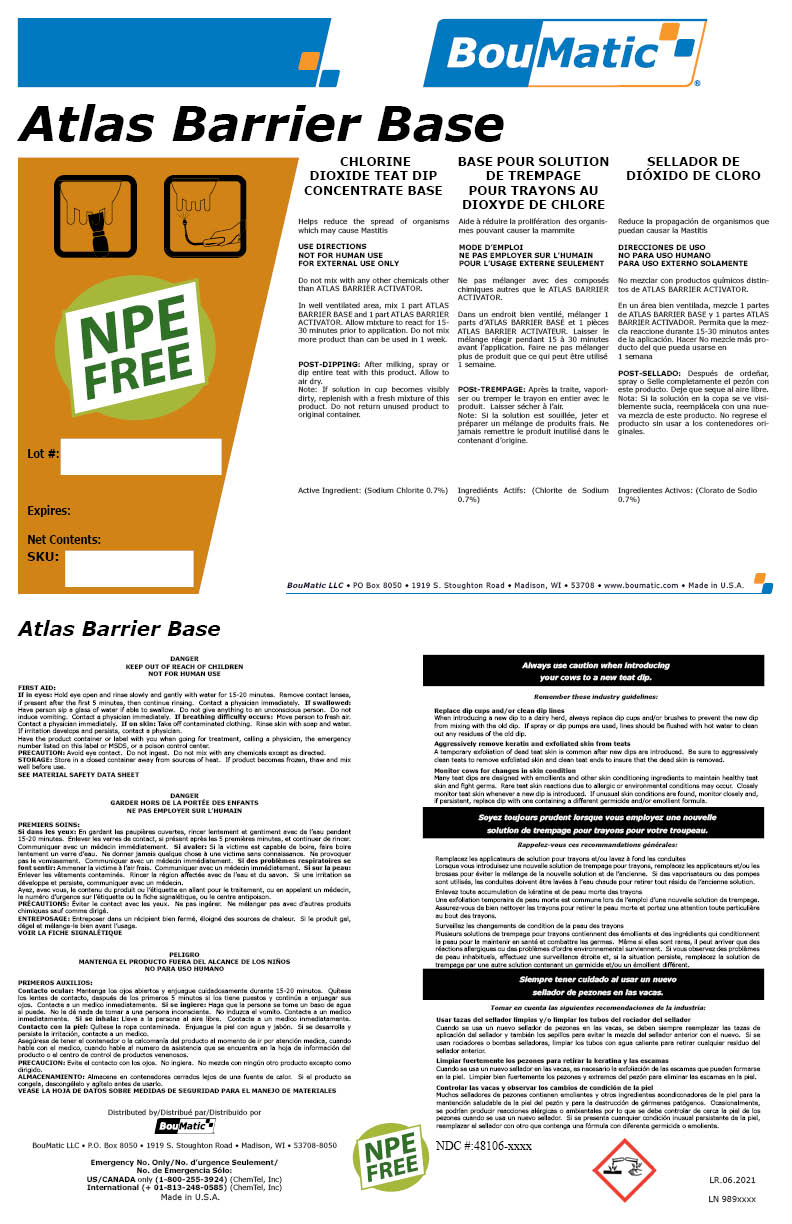 DRUG LABEL: Atlas Barrier Base
NDC: 48106-2054 | Form: LIQUID
Manufacturer: BOUMATIC, LLC
Category: animal | Type: OTC ANIMAL DRUG LABEL
Date: 20230310

ACTIVE INGREDIENTS: SODIUM CHLORITE 0.74 g/100 g

Atlas Barrier Base

Claim of effectiveness.

Helps reduce the spread of organisms
which may cause Mastitis

Use Directions

NOT FOR HUMAN USE
FOR EXTERNAL USE ONLY
Do not mix with any other chemicals other
than ATLAS BARRIER ACTIVATOR.
In well ventilated area, mix 1 part ATLAS
BARRIER BASE and 1 part ATLAS BARRIER
ACTIVATOR. Allow mixture to react for 15-
30 minutes prior to application. Do not mix
more product than can be used in 1 week.
POST-DIPPING: After milking, spray or
dip entire teat with this product. Allow to
air dry.
Note: If solution in cup becomes visibly
dirty, replenish with a fresh mixture of this
product. Do not return unused product to
original container.

First Aid

If in eyes: Hold eye open and rinse slowly and gently with water for at least 15 minutes. Remove contact
lenses, if present and easy to do. Continue rinsing. Contact a physician immediately. If swallowed:
Rinse mouth with water. Do not give anything to an unconscious person. Do not induce vomiting. Contact
a physician immediately. If Inhaled: Move person to fresh air. Contact a physician immediately. If
on skin: Immediatly remove contaminated clothing. Rinse skin with water. Use soap if available. Wash
clothes before reuse. If irritation develops and persists, contact a physician.
Have the product container or label with you when going for treatment, calling a physician, the emergency
number listed on this label or SDS, or a poison control center.

Precautions & Hazards

Avoid eye contact. Do not ingest. Do not mix with any chemicals except as directed.

General Storage

STORAGE: Store in a closed container away from sources of heat. If product becomes frozen, thaw and mix
well before use.